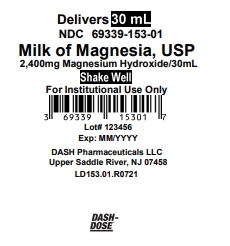 DRUG LABEL: milk of magnesia
NDC: 69339-153 | Form: SUSPENSION
Manufacturer: Natco Pharma USA LLC
Category: otc | Type: HUMAN OTC DRUG LABEL
Date: 20231101

ACTIVE INGREDIENTS: MAGNESIUM HYDROXIDE 2400 mg/30 mL
INACTIVE INGREDIENTS: WATER

Milk of Magnesia, USP Original Flavor DASH DOSE TM

Active Ingredient (in each 30 mL cup)

Magnesium hydroxide 2400 mg

Purpose

Saline laxative

Uses

As a Laxative

- relieves occasional constipation (irregularity)
- usually produces bowel movement in ½ to 6 hours

Warnings Do not use if you have ever had an allergic reaction to this product or any of its ingredients

Ask a doctor before use if you have

- kidney disease
- a magnesium-restricted diet
- stomach pain, nausea, or vomiting
- a sudden change in bowel habits that lasts over 14 days

Ask a doctor or pharmacist before use if you are taking a prescription drug.

This product may interact with certain prescription drugs.

Stop use and ask a doctor if

- you have rectal bleeding or no bowel movement after using this product. These could be signs of a serious condition.
- you need to use a laxative for more than 1 week

If pregnant or breast-feeding,

ask a health professional before use.

Keep out of reach of children.

In case of overdose, get medical help or contact a Poison Control Center right away (1-800-222-1222).

Directions

- shake well before use
- do not exceed the maximum recommended daily dose in a 24-hour period
- dose may be taken once a day preferably at bedtime, or as directed by a doctor
- drink a full glass (8 oz) of liquid with each dose

adults and children 12 years and older | 30ml, not more than 60ml in 24 hrs
children under 12 years of age | ask a doctor

Other information

- Each tablespoonful {15ml} contains: magnesium 500mg
- Sodium Content: not more than 324ppm
- Store at room temperature, 20-25°C (68-77°F). Avoid freezing.
- Original flavor
- sugar free, dye free, alcohol free, gluten free
- Do not use if lid seal is open or damaged
- See top of cup for lot number and expiration date

Inactive ingredient

purified water, sodium hypochlorite

How Supplied Milk of Magnesia, USP

2400mg/30ml is a white to offwhite liquid supplied as follows:
NDC 69339-153-01
(1) unit dose cup 30ml

NDC 69339-153-17
40 (4x10) unit dose cups 30ml

NDC 69339-153-19
100 (10x10) unit dose cups 30ml

Questions or comments?

201-786-6500

FOR INSTITUTIONAL USE ONLY

DASH

PHARMACEUTICALS

Distributed by: Dash Pharmaceuticals LLC

Upper Saddle RIver, NJ 07458

Principal Display Panel

Delivers 30 mL

NDC 69339-153-01

Milk of Magnesia, USP

2,400mg Magnesium Hydroxide/30mL

Shake Well

For Institutional Use Only

3 69339 15301 7

Lot# 123456

Exp: MM/YYYY

DASH Pharmaceuticals LLC

Upper Saddle River, NJ 07458

LD153.01.R0721

DASH-DOSE